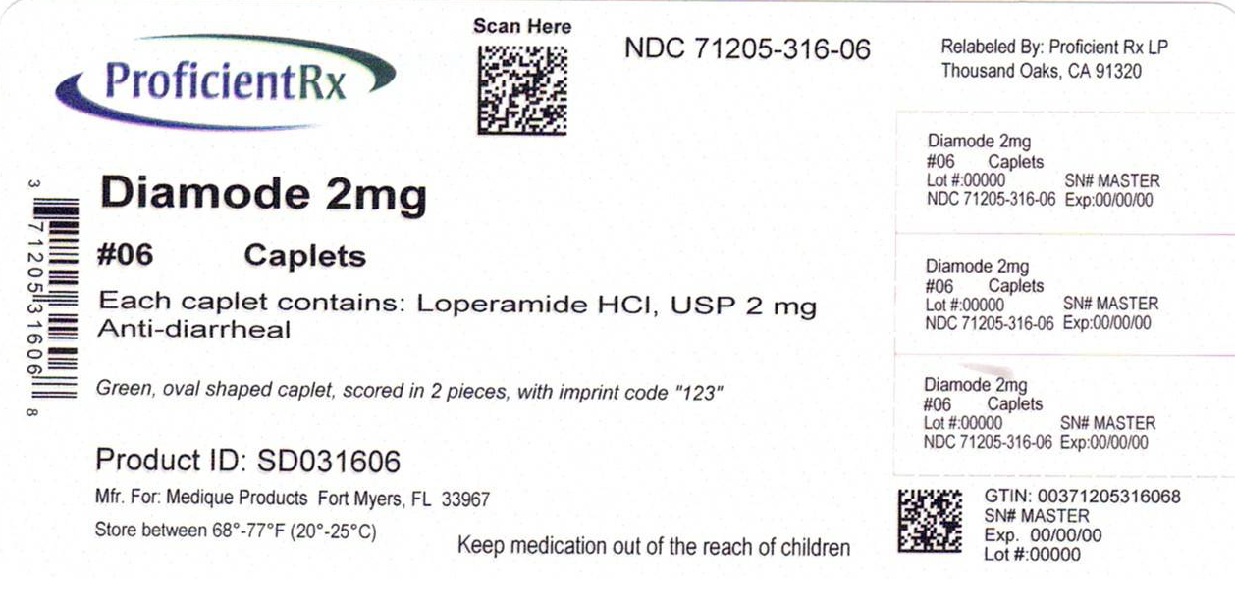 DRUG LABEL: MEDIQUE Diamode
NDC: 71205-316 | Form: TABLET
Manufacturer: Proficient Rx LP
Category: otc | Type: HUMAN OTC DRUG LABEL
Date: 20251001

ACTIVE INGREDIENTS: LOPERAMIDE HYDROCHLORIDE 2 mg/1 1
INACTIVE INGREDIENTS: ANHYDROUS LACTOSE; CROSCARMELLOSE SODIUM; CROSPOVIDONE (120 .MU.M); D&C YELLOW NO. 10; FD&C BLUE NO. 1; MAGNESIUM STEARATE; POWDERED CELLULOSE; STARCH, CORN; HYDROGENATED COTTONSEED OIL

MEDIQUE ® Diamode

Drug Facts

Active ingredient (in each caplet)

Loperamide HCl USP, 2mg

Purpose

Anti-diarrheal

Uses

Controls symptoms of diarrhea, including Travelers' Diarrhea.

Warnings

Allery alert:

Do not use if you have ever had a rash or other allergic reaction to loperamide HCl.

Heart alert:

Taking more than directed can cause serious heart problems or death.

Do not use

- if you have bloody or black stool

Ask a doctor before use if you have

- a fever
- mucus in the stool
- a history of liver disease

Ask a doctor or pharmacist before use if you are

- taking antibiotics

When using this product

- tiredness, drowsiness or dizziness may occur. Be careful when driving or operating machinery.

Stop use and ask a doctor if

- symptoms get worse
- diarrhea lasts more than 2 days
- you get abdominal swelling or bulging. These may be signs of a serious condition.

PREGNANCY OR BREAST FEEDING

If pregnant or breast feeding, ask a health professional before use.

Keep out of reach of children.

In case of overdose, get medical help or contact a Poison Control Center right away (1-800-222-1222).

Directions

- drink plenty of clear fluids to help prevent dehydration caused by diarrhea

Adults and children (12 years and over): Take 2 caplets after the first loose stool; 1 caplet after each subsequent loose stool; but no more than 4 caplets in 24 hours.

Children under 12 years: Do not give to children under 12 years of age.

Other information

- store between 68º - 77ºF (20º - 25ºC)
- tamper-evident sealed packets
- do not use any opened or torn packet
- see back of packet for lot number and expiration date

Inactive ingredients

anhydrous lactose, croscarmellose sodium, crospovidone, D&C Yellow # 10, FD&C Blue # 1, hydrogenated vegetable oil, magnesium stearate, powdered cellulose, pregelatinized starch

Questions or comments?

1-800-634-7680

Medique Diamode Label

Diamode

Controls the Symptoms of Diarrhea

Pull to Open

See New Warnings Information

Antidiarrheal • Loperamide HCl 2 mg

Relabeled by:

Proficient Rx LP

Thousand Oaks, CA 91320